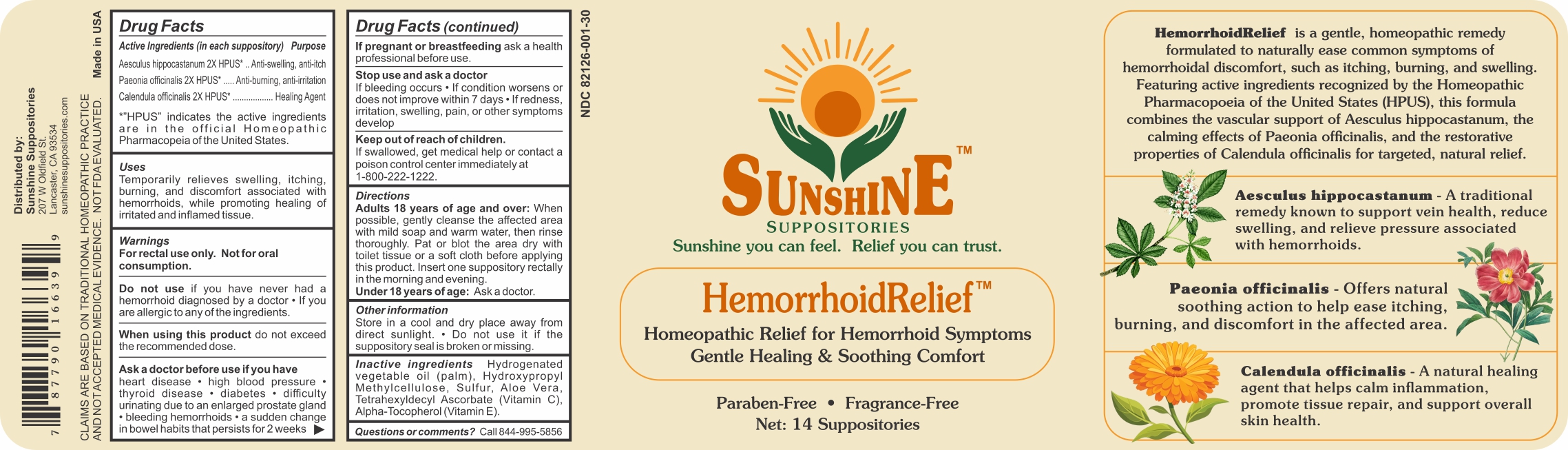 DRUG LABEL: Sunshine HemorrhoidRelief
NDC: 82126-001 | Form: SUPPOSITORY
Manufacturer: Apcco Labs, Inc
Category: homeopathic | Type: HUMAN OTC DRUG LABEL
Date: 20250618

ACTIVE INGREDIENTS: PAEONIA OFFICINALIS WHOLE 2 [hp_X]/1 mg; CALENDULA OFFICINALIS FLOWER 2 [hp_X]/1 mg; AESCULUS HIPPOCASTANUM WHOLE 2 [hp_X]/1 mg
INACTIVE INGREDIENTS: .ALPHA.-TOCOPHEROL ACETATE, DL-; SULFUR; HYDROGENATED PALM OIL; ALOE VERA LEAF; ASCORBYL TETRAISOPALMITATE; HYPROMELLOSE 2910 (15 MPA.S)

HemorrhoidRelief Apcco Labs

ACTIVE INGREDIENTS:

Aesculus Hippocastanum 2X HPUS* ….……………..…..……………………………………..…..…….Anti-swelling, anti-itch

Paeonia Officinalis 2X HPUS*.......…………..………….………..……..………...……………….… Anti-burning, anti-irritation

Calendula Officinalis 2X HPUS*.....………………………………………………………………………………....Healing Agent

*"HPUS" indicates the active ingredients are in the official Homeopathic Pharmacopeia of the United States.

PURPOSE:

.Anti-swelling, anti-itch

Anti-burning, anti-irritation

Healing Agent

INDICATIONS:

Temporarily relieves swelling, itching, burning, and discomfort associated with hemorrhoids, while promoting healing of irritated and inflamed tissue.

WARNINGS:

For rectal use only. Not for oral consumption.

Do not use if you have never had a hemorrhoid diagnosed by a doctor • If you are allergic to any of the ingredients.

When using this product, do not exceed the recommended dose.

Ask a doctor before use if you have heart disease • high blood pressure • thyroid disease•

diabetes • difficulty urinating due to an enlarged prostate gland • bleeding hemorrhoids • a sudden change in bowel habits that persists for 2 weeks

Stop use and ask a doctor.

If bleeding occurs • If condition worsens or does not improve within 7 days • If redness, irritation, swelling, pain, or other symptoms develop

If pregnant or breast feeding, ask a health professional before use.

KEEP OUT OF REACH OF CHILDREN:

If swallowed, get medical help or contact a poison control center immediately at 1-800-222-1222.

DIRECTIONS:

Adults 18 years of age and over: When possible, gently cleanse the affected area with mild soap and warm water, then rinse thoroughly. Pat or blot the area dry with toilet tissue or a soft cloth before applying this product. Insert one suppository rectally in the morning and evening.

Under 18 years of age: Ask a doctor.

INACTIVE INGREDIENTS:

Hydrogenated

vegetable oil (palm), Methylcellulose,

Hydroxypropyl

Sulfur, Aloe

Vera,

Tetrahexyldecyl Ascorbate (Vitamin C).

Alpha-Tocopherol (Vitamin

OTHER INFORMATION:

Store in a cool and dry place away from direct sunlight. • Do not use it if the suppository seal is broken or missing.

QUESTIONS:

Call 844-995-585